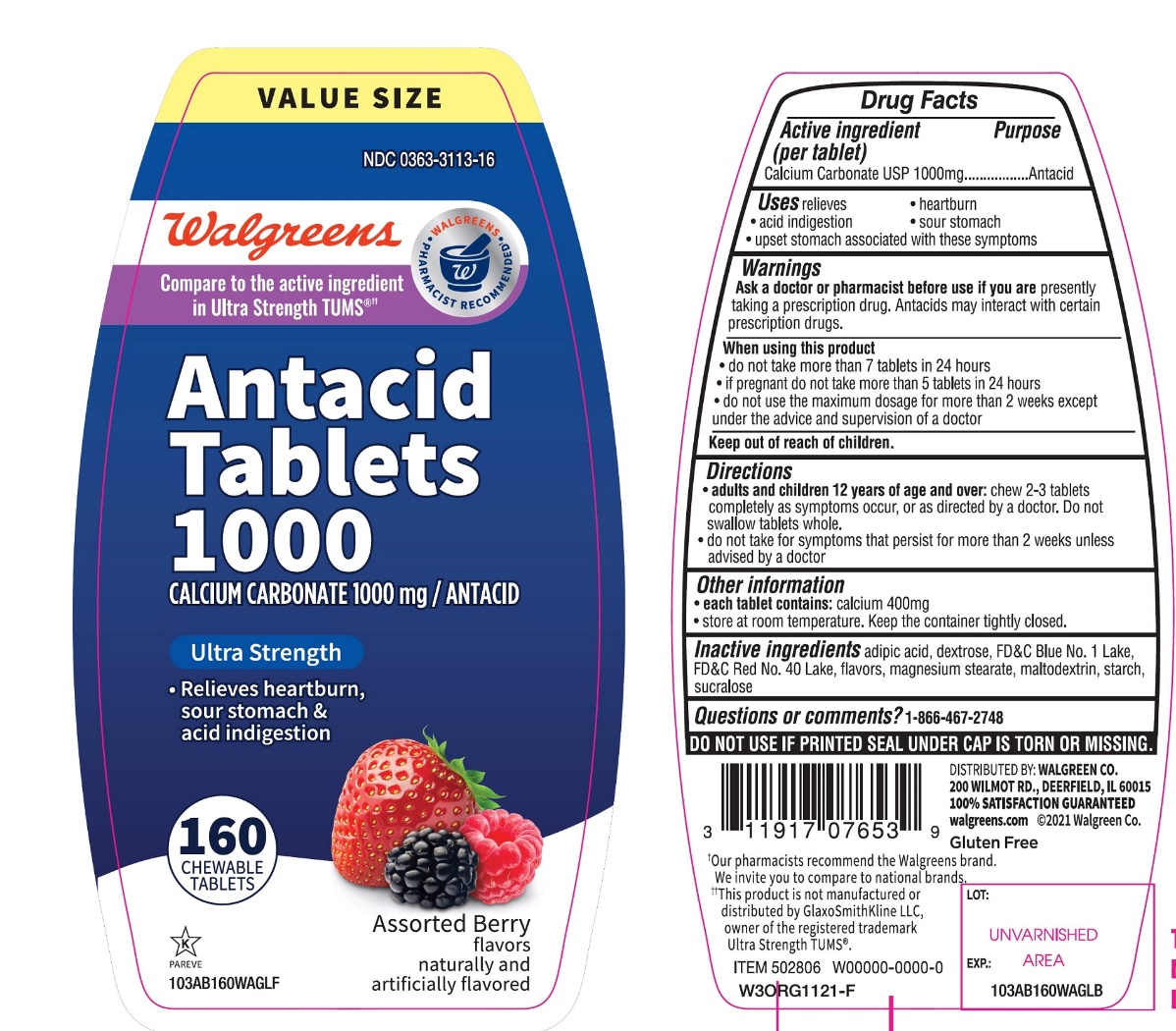 DRUG LABEL: Antacid Ultra Strength
NDC: 0363-3113 | Form: TABLET, CHEWABLE
Manufacturer: WALGREEN CO.
Category: otc | Type: HUMAN OTC DRUG LABEL
Date: 20251125

ACTIVE INGREDIENTS: CALCIUM CARBONATE 1000 mg/1 1
INACTIVE INGREDIENTS: ADIPIC ACID; DEXTROSE, UNSPECIFIED FORM; FD&C BLUE NO. 1; FD&C RED NO. 40; MAGNESIUM STEARATE; MALTODEXTRIN; STARCH, CORN; SUCRALOSE

Walgreens Ultra Strength 160 Chewable Tablets Assorted Berry Flavors

Active ingredient (per tablet)

Calcium Carbonate USP 1000mg

Purpose

Antacid

Uses

relieves:

- heartburn
- acid indigestion
- sour stomach
- upset stomach associated with these symptoms

Warnings

Ask a doctor or pharmacist before use if you arepresently taking a prescription drug. Antacids may interact with certain prescription drugs.

When using this product

- do not take more than 7 tablets in 24 hours
- If pregnant do not take more than 5 tablets in 24 hours
- do not use the maximum dosage for more than 2 weeks except under the advice and supervision of a doctor.

Directions

- adults and children 12 years of age and over: chew 2-3 tablets completely as symptoms occur, or as directed by a doctor. Do not swallow tablets whole.
- do not take for symptoms that persist for more than 2 weeks unless advised by a doctor

Other information

- each tablet contains: elemental calcium 400 mg
- Store at room temperature. Keep the container tightly closed.

Inactive ingredients

adipic acid, dextrose, FD&C Blue No. 1, FD&C Red No. 40, flavors, magnesium stearate, maltodextrin, , starch, sucralose,

Questions or comments?

1-866-467-2748

SAFETY SEALED: DO NOT USE IF PRINTED SEAL UNDER CAP IS TORN OR MISSING

Package/Label Principal Display Panel

Walgreens

Compare to TUMS®active ingredients††

NDC0363-3113-16

Antacid Tablets 1000

CALCIUM CARBONATE 1000mg/ ANTACID

ULTRA STRENGTH

- Relieves heartburn, sour stomach & acid indigestion

ASSORTED BERRY FLAVORS

160 CHEWABLE TABLETS

Walgreens Pharmacist Recommended

Walgreens Pharmacist Survey

DISTRIBUTED BY: WALGREEN CO.

200 WILMOT RD., DEERFIELD, IL 60015

100 % SATISFACTION GUARANTEED

walgreens.com ©2017 Walgreen Co.

††This product is not manufactured or distributed by GlaxoSmithKline, the distributor of TUMS®.

ORG1217-F REV 0119